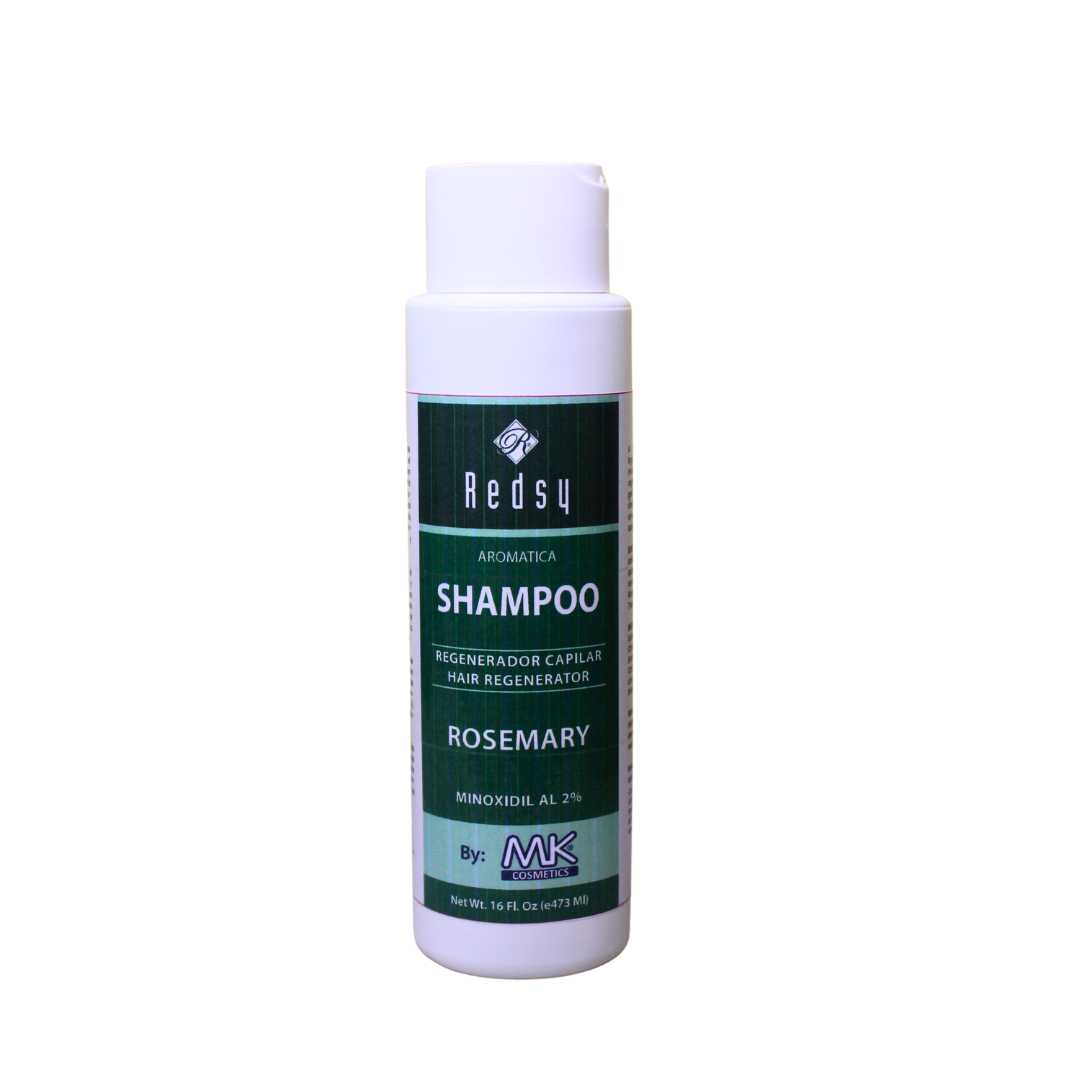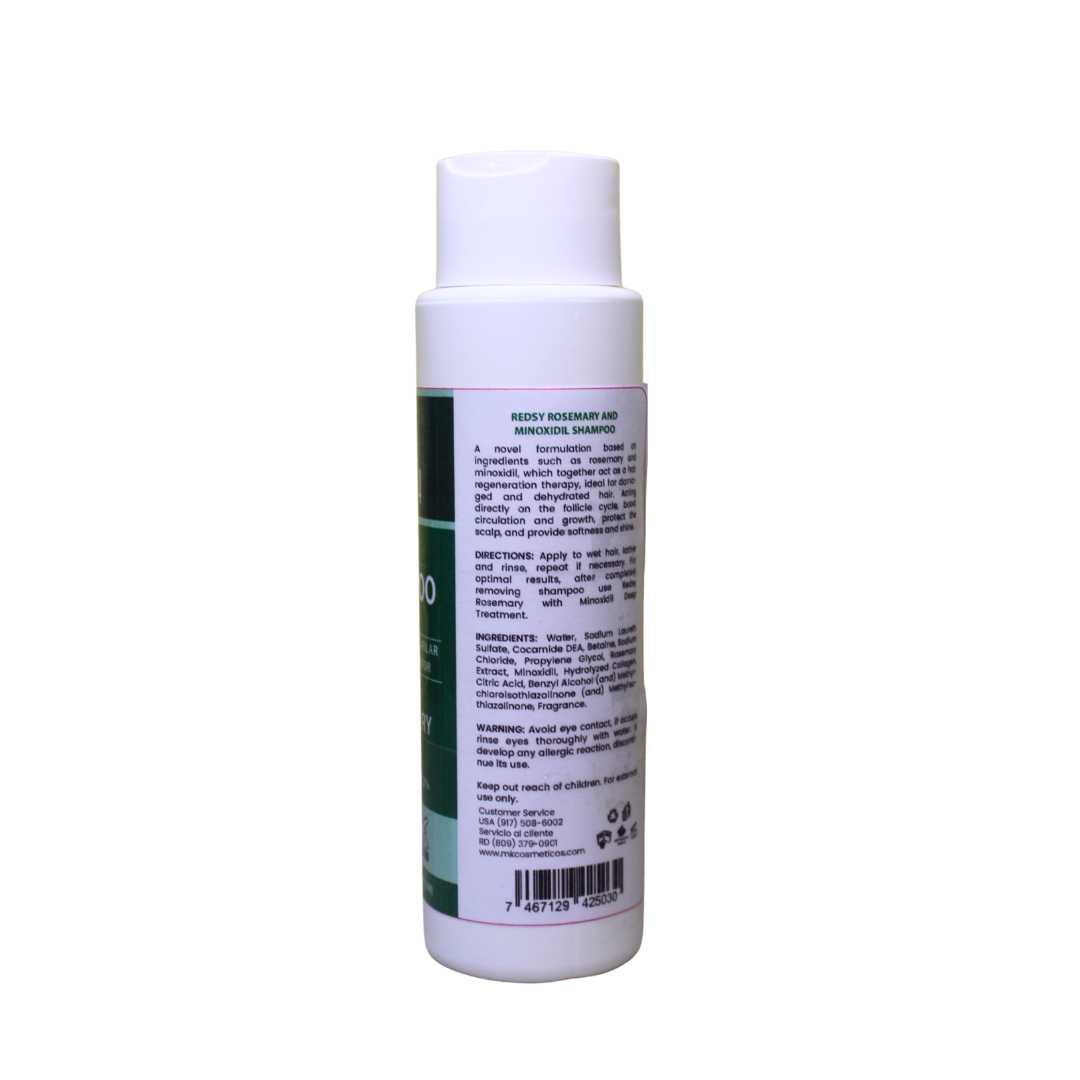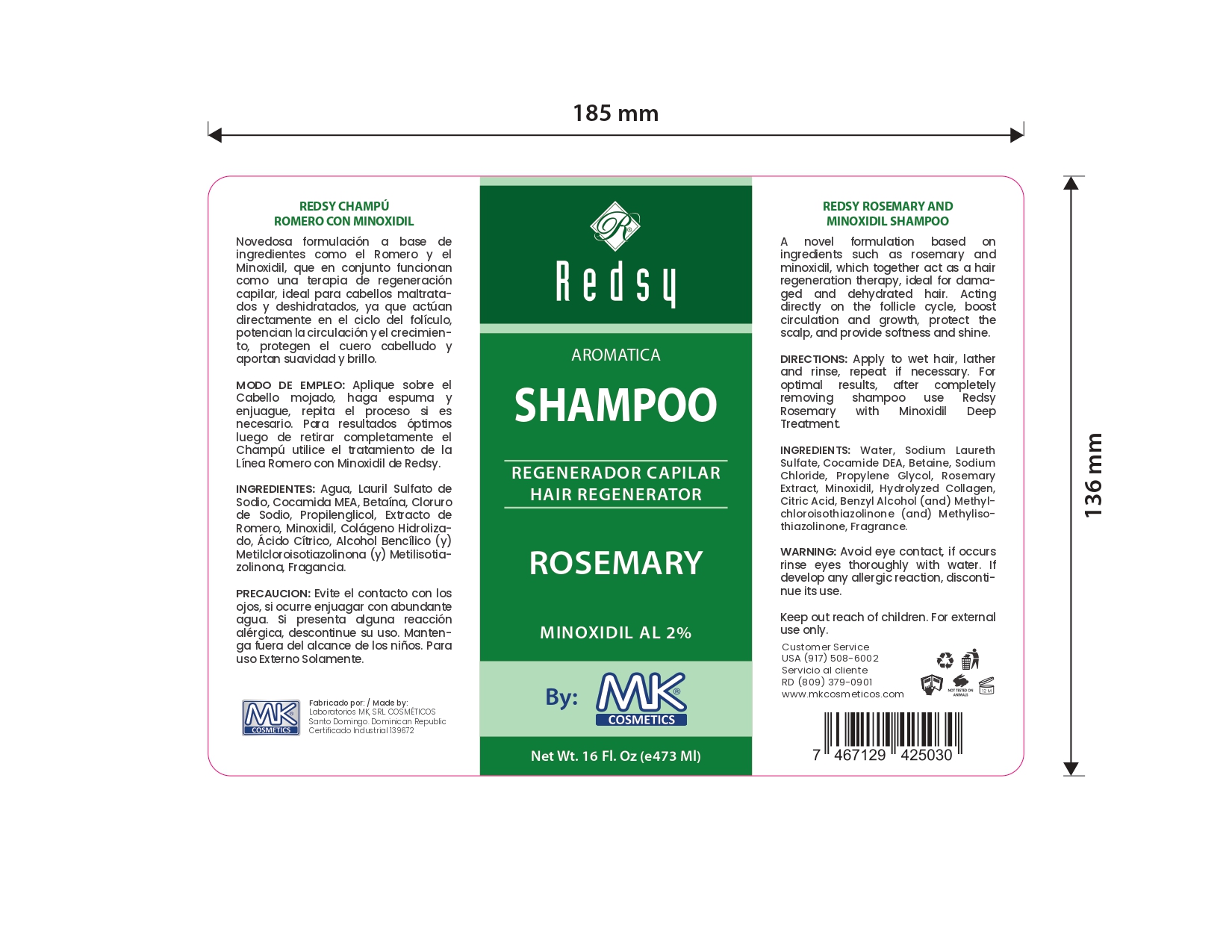 DRUG LABEL: aromatica hair champu
NDC: 87022-011 | Form: SHAMPOO
Manufacturer: LABORATORIO MK SRL
Category: otc | Type: HUMAN OTC DRUG LABEL
Date: 20250926

ACTIVE INGREDIENTS: MINOXIDIL 2 mg/473 mL
INACTIVE INGREDIENTS: HYDROLYZED PORCINE COLLAGEN (ENZYMATIC; 3000 MW); METHYLISOTHIAZOLINONE; WATER; SODIUM LAURETH SULFATE; COCAMIDE DEA; PROPYLENE GLYCOL 1,2-DISTEARATE; CITRIC ACID; METHYLCHLOROISOTHIAZOLINONE; SODIUM CHLORIDE; BETAINE; BENZYL ALCOHOL; ROSEMARY OIL

INDICATIONS AND USAGE

Apply to wet hair, lather and rinse, repeat if necessary.

INACTIVE INGREDIENT

Water, Sodium Laureth Sulfate, Cocamide DEA, Betaine, Sodium Chloride, Propylene Glycol, Rosemary Extract, Hydrolyzed Collagen, Citric Acid, Benzyl Alcohol (and) Methylchloroisothiazolinone (and) Methylisothiazolinone, Fragrance.

WARNINGS

Avoid eye contact, if occurs rinse eyes thoroughly with water. If develop any allergic reaction, discontinue its use. Keep out reach of children. For external use only.

INFORMATION FOR OWNERS/CAREGIVERS

Customer Service USA (917)508-6002

Customer Service RD (809)379-0900

www.mkcosmeticos.com

DOSAGE AND ADMINISTRATION

Apply to wet hair, lather and rinse, repeat if necessary.

KEEP OUT OF REACH OF CHILDREN

Keep out reach of children. For external use only.

PURPOSE

Aromatica hair regenerator

PACKAGE LABEL

Aromatica Hair regenerator